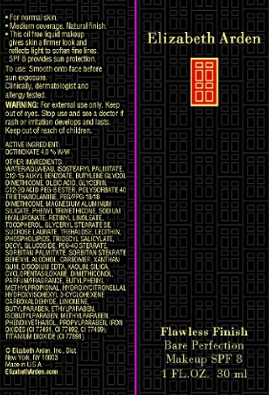 DRUG LABEL: Flawless Finish Bare Perfection Makeup SPF 8 Beige
NDC: 67938-0830 | Form: LOTION
Manufacturer: Elizabeth Arden, Inc
Category: otc | Type: HUMAN OTC DRUG LABEL
Date: 20110506

ACTIVE INGREDIENTS: OCTINOXATE 1.1988 mL/30 mL
INACTIVE INGREDIENTS: WATER; TITANIUM DIOXIDE; BUTYLENE GLYCOL; ALKYL (C12-15) BENZOATE; DIMETHICONE; OLEIC ACID; GLYCERIN; POLYSORBATE 40; MAGNESIUM ALUMINUM SILICATE; TROLAMINE; PHENYL TRIMETHICONE; KAOLIN; XANTHAN GUM; PHENOXYETHANOL; SUCROSE LAURATE; DICAPRYLYL CARBONATE; GLYCERYL MONOSTEARATE; METHYLPARABEN; DOCOSANOL; PROPYLPARABEN; SORBITAN MONOPALMITATE

BC0830

DESCRIPTION

For normal skin. Medium coverage. Natural finish. This oil free liquid makeup gives skin a firmer look and reflects light to soften fine lines. SPF 8 provides sun protection. Clinically, dermatologist and allergy tested.

INDICATIONS AND USAGE

To Use: Smooth on to face before sun exposure.

WARNINGS

Warning: For external use only. Keep out of eyes.Stop use and see a doctor is rash or irritation develops and lasts. Keep out of reach of children.

OTC - ACTIVE INGREDIENT

Active Ingredient: Octinoxate 4.0% w/w.

INACTIVE INGREDIENT

Other Ingredients: Water/Aqua/Eau, Isostearyl Palmitate, C12-15 Alkyl Benzoate, Butylene Glycol, Dimethicone, Oleic Acid, Glycerin, C12-20 Acid PEG-8 Ester, Polysorbate 40, Triethanolamine, Magnesium Aluminum Silicate, Dimethicone Copolyol, Phenyl Trimethicone, Sodium Hyaluronate, Retinyl Linoleate, Tocopherol, Glyceryl Stearate SE, Sucrose Laurate, Trehalose, Lecithin, Phospholipids, Tridecyl Salicylate, Decyl Glucoside, PEG-40 Stearate, Sorbitan Palmitate, Sorbitan Stearate, Behenyl Alcohol, Carbomer, Xanthan Gum, Disodium EDTA, Kaolin, Silica, Cyclopentasiloxane, Dimethiconol, Parfum/Fragrance, Butylphenyl Methylpropional, Hydroxycitronellal, Hydroxyisohexyl 3-Cyclohexene Carboxaldehyde, Limonene, Butylparaben, Ethylparaben, Isobutylparaben, Methylparaben, Phenoxyethanol, Propylparaben, Iron Oxides (CI77491, CI 77492, CI 77499), Titanium Dioxide (CI 77891).

DOSAGE & ADMINISTRATION

Smooth on to face.

OTC - KEEP OUT OF REACH OF CHILDREN

Keep out of reach of children.

OTC - PURPOSE

SPF 8 provides sun protection.

OTC - WHEN USING

Keep out of eyes.